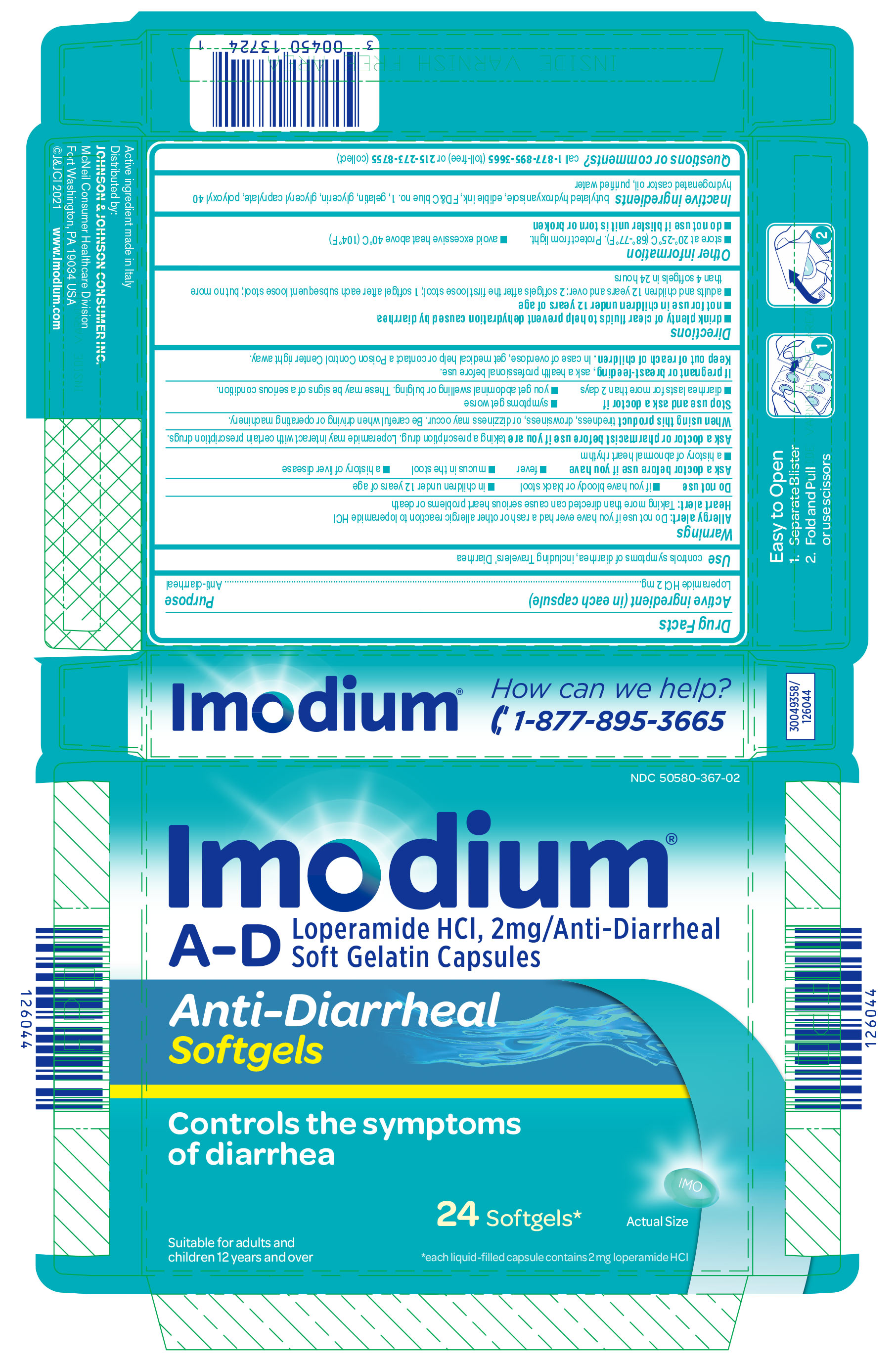 DRUG LABEL: Imodium A-D
NDC: 50580-367 | Form: CAPSULE, LIQUID FILLED
Manufacturer: Kenvue Brands LLC
Category: otc | Type: HUMAN OTC DRUG LABEL
Date: 20251222

ACTIVE INGREDIENTS: LOPERAMIDE HYDROCHLORIDE 2 mg/1 1
INACTIVE INGREDIENTS: BUTYLATED HYDROXYANISOLE; FD&C BLUE NO. 1; GELATIN, UNSPECIFIED; GLYCERIN; GLYCERYL MONOCAPRYLATE; POLYOXYL 40 HYDROGENATED CASTOR OIL; WATER

Imodium A-D

Drug Facts

Active ingredient (in each capsule)

Loperamide HCl 2 mg

Purpose

Anti-diarrheal

Use

controls symptoms of diarrhea, including Travelers' Diarrhea

Warnings

Allergy alert: Do not use if you have ever had a rash or other allergic reaction to loperamide HCl

Heart alert: Taking more than directed can cause serious heart problems or death

Do not use

- if you have bloody or black stool
- in children under 12 years of age

Ask a doctor before use if you have

- fever
- mucus in the stool
- a history of liver disease
- a history of abnormal heart rhythm

Ask a doctor or pharmacist before use if you are taking a prescription drug. Loperamide may interact with certain prescription drugs.

When using this product tiredness, drowsiness, or dizziness may occur. Be careful when driving or operating machinery.

Stop use and ask a doctor if

- symptoms get worse
- diarrhea lasts for more than 2 days
- you get abdominal swelling or bulging. These may be signs of a serious condition.

If pregnant or breast-feeding, ask a health professional before use.

Keep out of reach of children. In case of overdose, get medical help or contact a Poison Control Center right away.

Allergy alert

Do not use if you have ever had a rash or other allergic reaction to loperamide HCl

Heart alert

Taking more than directed can cause serious heart problems or death

Do not use

- if you have bloody or black stool
- in children under 12 years of age

Ask a doctor before use if you have

- fever
- mucus in the stool
- a history of liver disease
- a history of abnormal heart rhythm

Ask a doctor or pharmacist before use if you are taking a prescription drug. Loperamide may interact with certain prescription drugs.

When using this product tiredness, drowsiness, or dizziness may occur. Be careful when driving or operating machinery.

Stop use and ask a doctor if

- symptoms get worse
- diarrhea lasts for more than 2 days
- you get abdominal swelling or bulging. These may be signs of a serious condition.

PREGNANCY OR BREAST FEEDING

If pregnant or breast-feeding, ask a health professional before use.

Keep out of reach of children. In case of overdose, get medical help or contact a Poison Control Center right away.

Directions

- drink plenty of clear fluids to help prevent dehydration caused by diarrhea
- not for use in children under 12 years of age
- adults and children 12 years and over: 2 softgels after the first loose stool; 1 softgel after each subsequent loose stool; but no more than 4 softgels in 24 hours

Other information

- store at 20°-25°C (68°-77°F). Protect from light.
- avoid excessive heat above 40°C (104°F)
- do not use if blister unit is torn or broken

Inactive ingredients

butylated hydroxyanisole, edible ink, FD&C blue no. 1, gelatin, glycerin, glyceryl caprylate, polyoxyl 40 hydrogenated castor oil, purified water

Questions or comments?

call 1-877-895-3665 (toll-free) or 215-273-8755 (collect)

PRINCIPAL DISPLAY PANEL

NDC 50580-367-02

Imodium®
A-D
Loperamide HCl, 2mg/Anti-Diarrheal
Soft Gelatin Capsules

Anti-Diarrheal
Softgels

Controls the symptoms
of diarrhea

Suitable for adults and
children 12 years and over

24 Softgels*
Actual Size

*each liquid-filled capsule contains 2 mg loperamide HCl